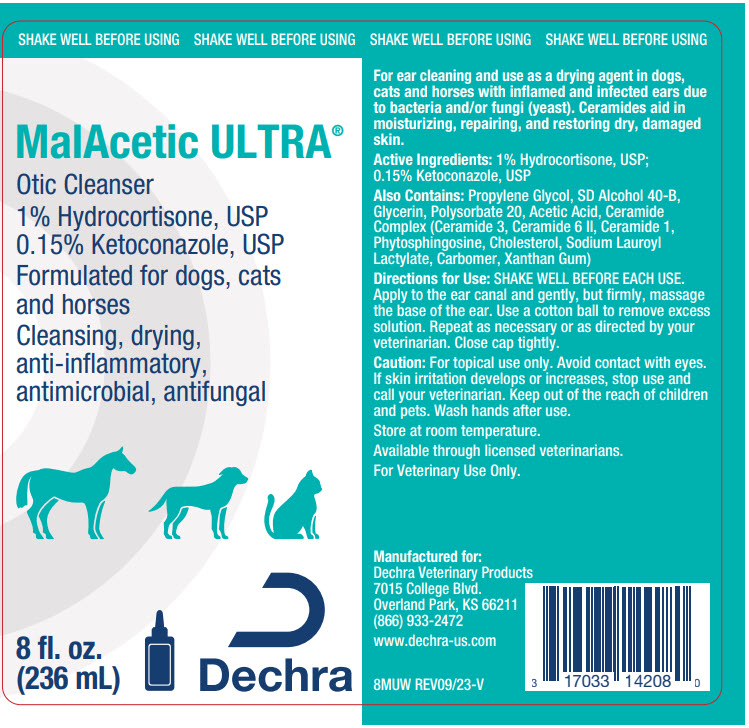 DRUG LABEL: Malacetic Ultra Otic Cleanser
NDC: 17033-142 | Form: LIQUID
Manufacturer: Dechra Veterinary Products
Category: animal | Type: OTC ANIMAL DRUG LABEL
Date: 20240403

ACTIVE INGREDIENTS: Hydrocortisone 10 mg/1 mL; Ketoconazole 1.5 mg/1 mL

MALACETIC ULTRA®
Otic Cleanser

VETERINARY INDICATIONS

For ear cleaning and use as a drying agent in dogs, cats and horses with inflamed and infected ears due to bacteria and/or fungi (yeast). Ceramides aid in moisturizing, repairing, and restoring dry, damaged skin.

DESCRIPTION

Active Ingredients: 1% Hydrocortisone, USP; 0.15% Ketoconazole, USP

Also Contains: Propylene Glycol, SD Alcohol 40-B, Glycerin, Polysorbate 20, Acetic Acid, Ceramide Complex (Ceramide 3, Ceramide 6 II, Ceramide 1, Phytosphingosine, Cholesterol, Sodium Lauroyl Lactylate, Carbomer, Xanthan Gum)

DOSAGE AND ADMINISTRATION

Directions for Use: SHAKE WELL BEFORE EACH USE. Apply to the ear canal and gently, but firmly, massage the base of the ear. Use a cotton ball to remove excess solution. Repeat as necessary or as directed by your veterinarian. Close cap tightly.

WARNINGS

Caution: For topical use only. Avoid contact with eyes. If skin irritation develops or increases, stop use and call your veterinarian. Keep out of the reach of children and pets. Wash hands after use.

STORAGE AND HANDLING

Store at room temperature.

Available through licensed veterinarians.

For Veterinary Use Only.

Manufactured for:
Dechra Veterinary Products
7015 College Blvd.
Overland Park, KS 66211
(866) 933-2472

www.dechra-us.com

8MUW REV09/23-V

PRINCIPAL DISPLAY PANEL - 236 mL Bottle Label

SHAKE WELL BEFORE USING

MalAcetic ULTRA®

Otic Cleanser
1% Hydrocortisone, USP
0.15% Ketoconazole, USP
Formulated for dogs, cats
and horses
Cleansing, drying,
anti-inflammatory,
antimicrobial, antifungal

8 fl. oz.
(236 mL)

Dechra